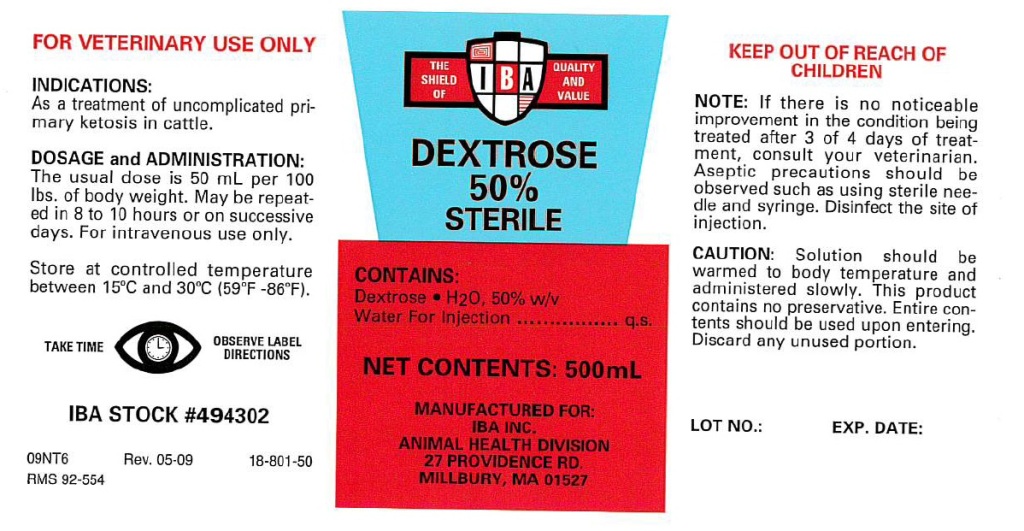 DRUG LABEL: Dextrose
NDC: 29983-2403 | Form: INJECTION, SOLUTION
Manufacturer: IBA Inc.
Category: animal | Type: OTC ANIMAL DRUG LABEL
Date: 20180116

ACTIVE INGREDIENTS: DEXTROSE MONOHYDRATE 250 g/500 mL

DEXTROSE 50%

INDICATIONS:

As a treatment of uncomplicated pri-
mary ketosis in cattle.

DOSAGE and ADMINISTRATION:

The usual dose is 50 mL per 100
lbs. of body weight. May be repeat-
ed in 8 to 10 hours or on successive
days. For intravenous use only.

FOR VETERINARY USE ONLY

STORAGE AND HANDLING

Store at controlled temperature
between 15°C and 30°C (59°F -86°F).

WARNINGS AND PRECAUTIONS

TAKE TIME OBSERVE LABEL DIRECTIONS

CONTAINS:

Dextrose • H2O, 50% w/v
Water For Injection ....................... q.s.

KEEP OUT OF REACH OF CHILDREN

NOTE:

If there is no noticeable
improvement in the condition being
treated after 3 of 4 days of treat-
ment, consult your veterinarian.
Aseptic precautions should be
observed such as using sterile nee-
dle and syringe. Disinfect the site of
injection.

CAUTION:

Solution should be
warmed to body temperature and
administered slowly. This product
contains no preservative. Entire con-
tents should be used upon entering.
Discard any unused portion.

INFORMATION FOR OWNERS/CAREGIVERS

IBA STOCK #494302

09NT6

Rev. 05-09

18-801-50

RMS 92-554

STERILE

NET CONTENTS: 500 mL

MANUFACTURED FOR:
IBA INC.
ANIMAL HEALTH DIVISION
27 PROVIDENCE RD.
MILLBURY, MA 01527

LOT NO.:

EXP. DATE: